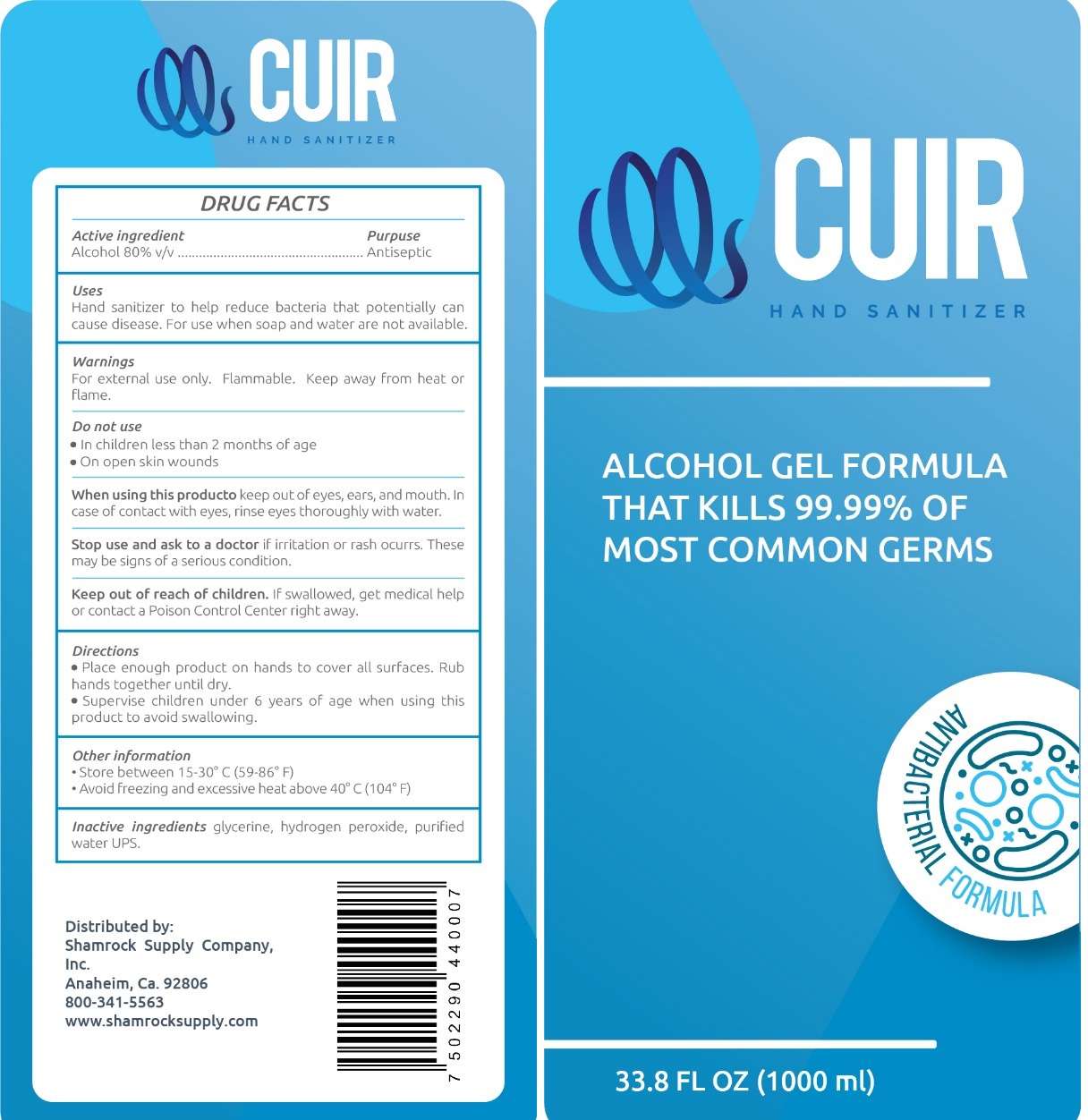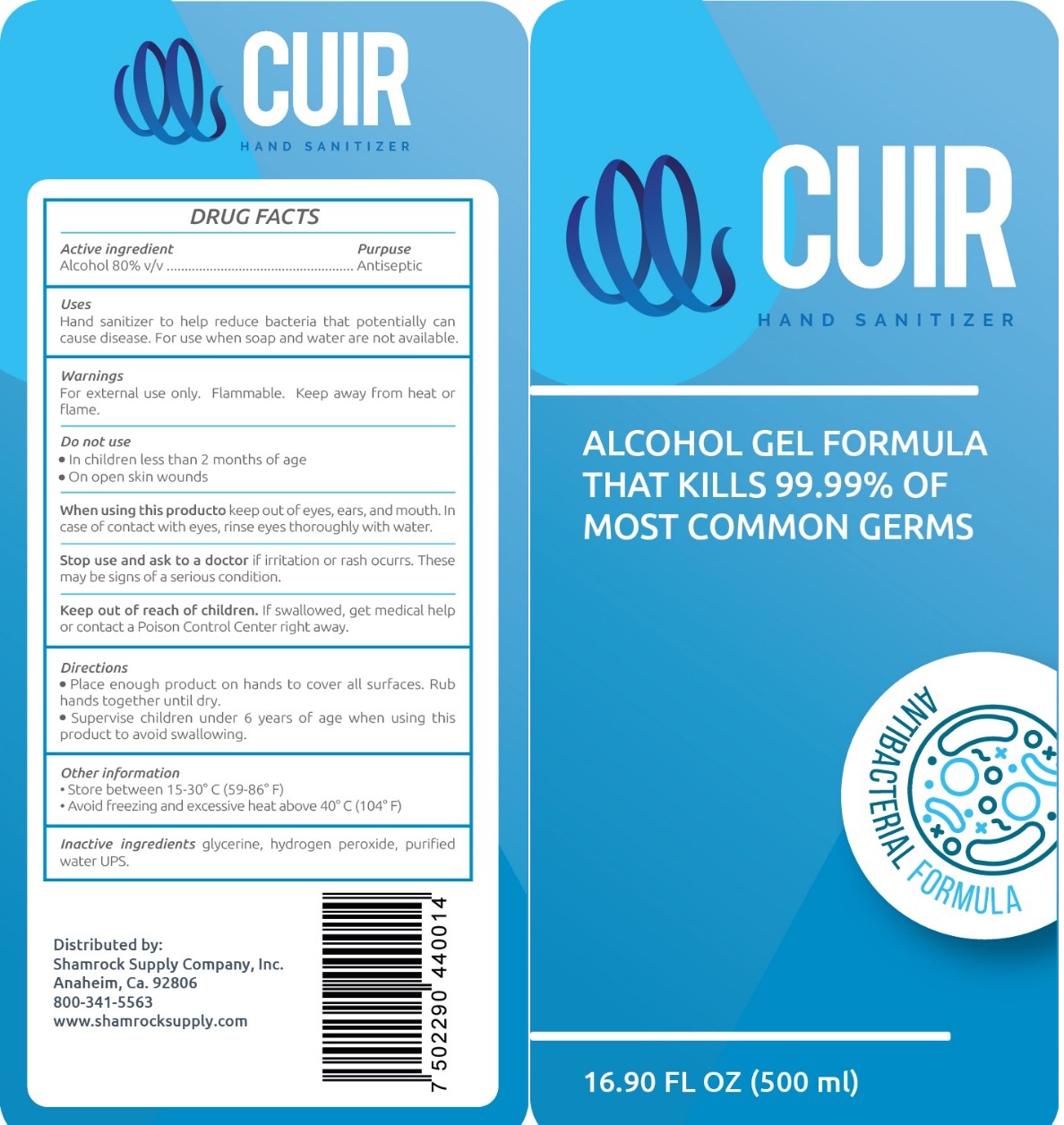 DRUG LABEL: CUIR Hand Sanitizer
NDC: 78514-000 | Form: GEL
Manufacturer: Comercial Riley S.A. de C.V.
Category: otc | Type: HUMAN OTC DRUG LABEL
Date: 20220225

ACTIVE INGREDIENTS: ALCOHOL 0.8 mL/1 mL
INACTIVE INGREDIENTS: GLYCERIN; HYDROGEN PEROXIDE; WATER

CUIR Hand Sanitizer

Active ingredient

Alcohol 80% v/v

Purpose

Antiseptic

Uses

Hand sanitizer to help reduce bacteria that potentially can cause disease. For use when soap water are not available.

Warnings

For external use only. Flammable. Keep away from heat or flame.

Do not use

- In chilren less than 2 months of age
- On open skin wounds

When using this producto

keep out of eyes, and mouth. In case of contact with eyes, rinse eyes thoroughly with water.

Stop use and ask to a doctor

if irritation or rash occurs. These may be signs of serious condition.

Keep out of reach of children.

If swallowed, get medical help or contact a Poison Control Center right away.

Directions

- Place enough product on hands to cover all surfaces. Rub hands together until dry.
- Supervise children under 6 years of age when using this product to avoid swallowing.

Other information

- Store between 15-30° C (59-86° F)
- Avoid freezing and excessive heat above 40°C (104° F)

Inactive ingredients

glycerine, hydregen peroxide, purifed water UPS.